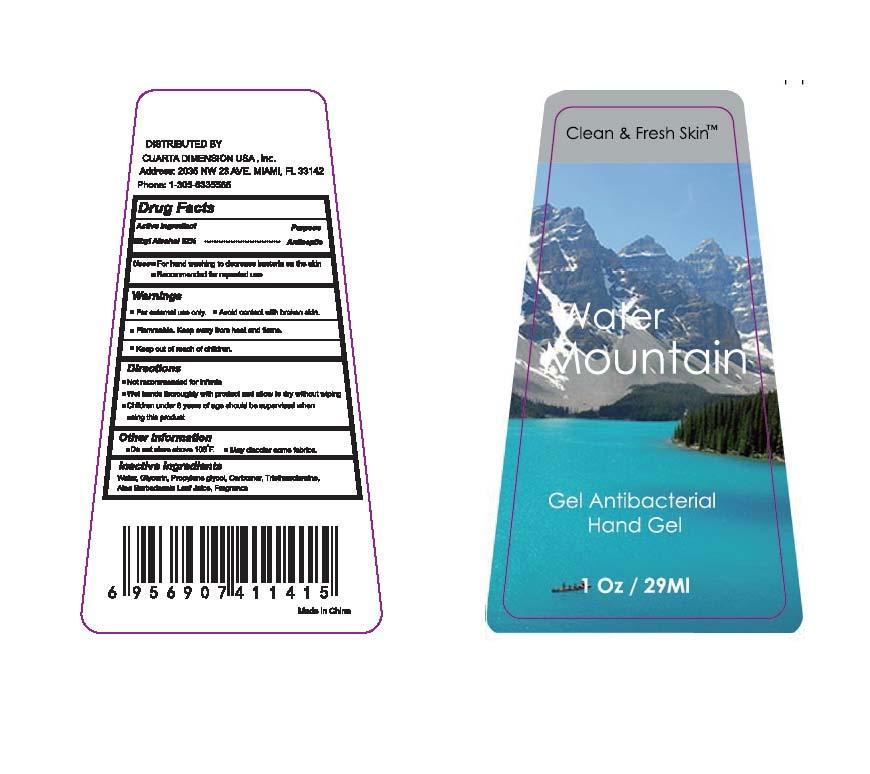 DRUG LABEL: Water Mountain Hand Sanitizer
NDC: 52979-8006 | Form: GEL
Manufacturer: CUARTA DIMENSION USA, INC.
Category: otc | Type: HUMAN OTC DRUG LABEL
Date: 20120818

ACTIVE INGREDIENTS: Alcohol 62 mL/100 mL
INACTIVE INGREDIENTS: WATER; GLYCERIN; PROPYLENE GLYCOL; CARBOMER HOMOPOLYMER TYPE C (ALLYL PENTAERYTHRITOL CROSSLINKED); TROLAMINE; ALOE VERA LEAF

Active ingredient
Ethyl Alcohol 62%

Purpose
Antiseptic

Uses
For hand washing to decrease bacteria on the skin
Recommended for repeated use

Warnings
For external use only.
Avoid contact with broken skin.
Flammable. Keep away from heat and flame.
Keep out of reach of children.

Keep out of reach of children.
Children under 6 of age should be supervised when using this product.

Directions
Not recommanded for infants
Wet hands thoroughly with product and allow to dry without wiping
Children under 6 of age should be supervised when using this product.
Other Information
Do not store above 105 degrees F.
May discolor some fabrics.

Inactive Ingredients
Water, Glycerin, Propylene Glycol, Carbomer, Triethanolamine, Aloe Barbadensis Leaf Juice, Fragrance